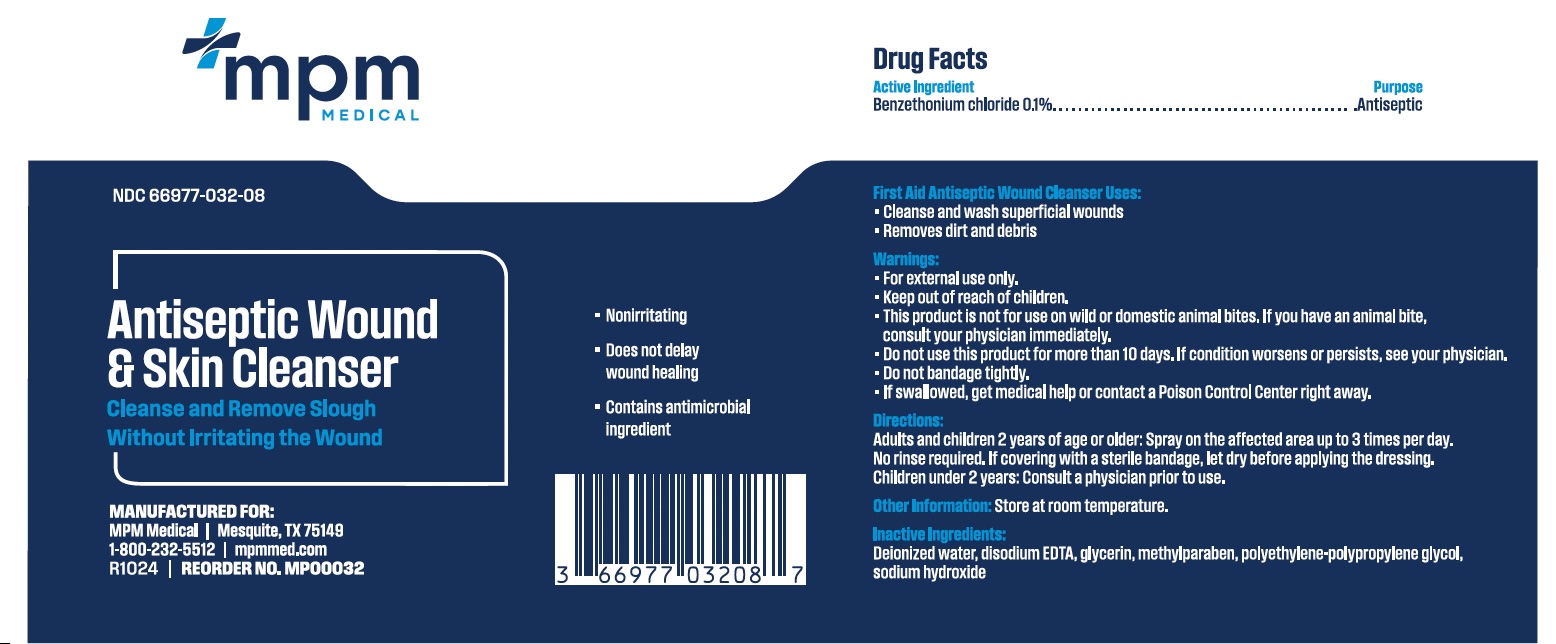 DRUG LABEL: Antiseptic
NDC: 66977-032 | Form: SOLUTION
Manufacturer: MPM Medical, LLC
Category: otc | Type: HUMAN OTC DRUG LABEL
Date: 20251229

ACTIVE INGREDIENTS: BENZETHONIUM CHLORIDE 1 mg/1 mL
INACTIVE INGREDIENTS: EDETATE DISODIUM; GLYCERIN; METHYLPARABEN; POLOXAMER 188; SODIUM HYDROXIDE; WATER

MP00032 MPM Antiseptic Wound & Skin Cleanser 8 fl.oz

Active Ingredient

Benzethonium chloride 0.1%

Purpose

Antiseptic

Uses

- To clean superficial wounds
- For washing small superfical wounds
- Aids in removal of foreign material such as dirt and debris
- First-aid product

Warnings

For external use only. Keep out of reach of children.

This product is not for use on wild or domestic animal bites. If you have an animal bite, consult your physician immediately.

Do not use this product for more than 10 days. If condition worsens or persists, see your physician.

Do not bandage tightly.

If swallowed, get medical help or contact a Poison Control Center right away.

Keep out of reach of children

Directions

Apply to affected area.

Adults and children 2 years of age or older: Spray on the affected area up to 3 times per day.

May be covered with a sterile bandage, if bandaged let dry first.

Children under 2 years: Consult a physician prior to use.

Other information

Store at room temperature

Inactive ingredients

Deionized water, disodium EDTA, glycerin, methylparaben, polyethylene-polypropylene glycol, sodium hydroxide